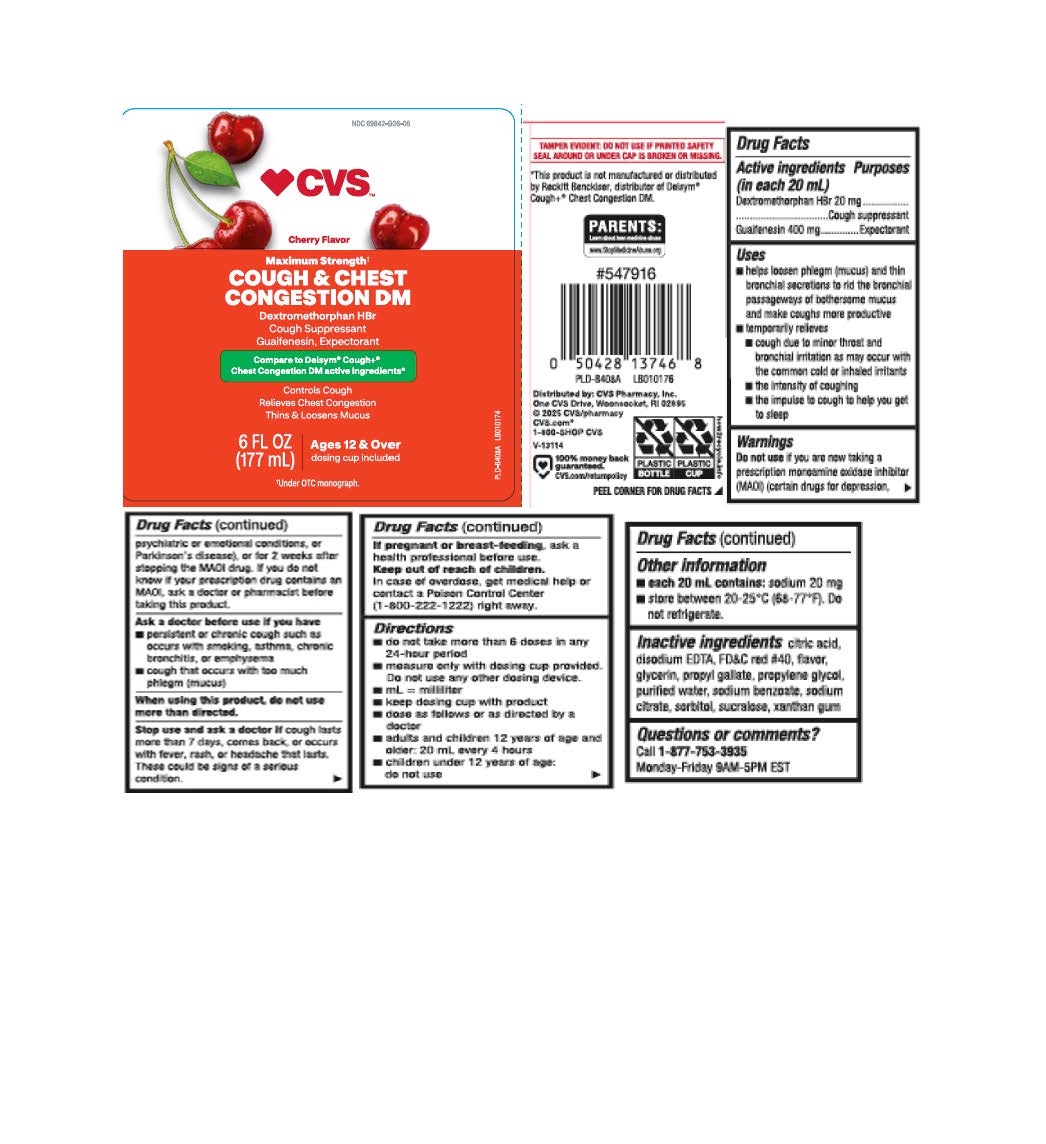 DRUG LABEL: Cough and Chest Congestion DM
NDC: 69842-926 | Form: LIQUID
Manufacturer: CVS Pharmacy
Category: otc | Type: HUMAN OTC DRUG LABEL
Date: 20250818

ACTIVE INGREDIENTS: DEXTROMETHORPHAN HYDROBROMIDE 20 mg/20 mL; GUAIFENESIN 400 mg/20 mL
INACTIVE INGREDIENTS: ANHYDROUS CITRIC ACID; GLYCERIN; PROPYLENE GLYCOL; WATER; SUCRALOSE; XANTHAN GUM; FD&C RED NO. 40; SODIUM CITRATE; SORBITOL; EDETATE CALCIUM DISODIUM; SODIUM BENZOATE; PROPYL GALLATE

Drug Facts

Active ingredients (in each 20 mL)

Dextromethorphan HBr 20 mg

Guaifenesin 400 mg

Purposes

Cough suppressant

Expectorant

Uses

- helps loosen phlegm (mucus) and thin bronchial secretions to rid the bronchial passageways of bothersome mucus and make coughs more productive
- temporarily relieves
  - cough due to minor throat and bronchial irritation as may occur with the common cold or inhaled irritants
  - the intensity of coughing
  - the impulse to cough to help you get to sleep

Warnings

Do not use

if you are now taking a prescription monoamine oxidase inhibitor (MAOI) (certain drugs for depression, psychiatric or emotional conditions, or Parkinson's disease), or for 2 weeks after stopping the MAOI drug. If you do not know if your prescription drug contains an MAOI, ask a doctor or pharmacist before taking this product.

Ask a doctor before use if you have

- persistent or chronic cough such as occurs with smoking, asthma, chronic bronchitis, or emphysema
- cough that occurs with too much phlegm (mucus)

When using this product,

do not use more than directed.

Stop use and ask a doctor if

cough lasts more than 7 days, comes back, or occurs with fever, rash or headache that lasts. These could be signs of a serious condition.

If pregnant or breast-feeding,

ask a health professional before use.

Keep out of reach of children

In case of overdose, get medical help or contact a Poison Control Center (1-800-222-1222) right away.

Directions

- do not take more than 6 doses in any 24-hour period
- measure only with dosing cup provided. Do not use any other dosing device.
- keep dosing cup with product
- dose as follows or as directed by a doctor
- mL= milliliter
- adults and children 12 years of age and older: 20 mL every 4 hours
- children under 12 years of age: do not use

Other information

- each 20 mL contains: sodium 20 mg
- store between 20-25ºC (68º-77ºF). Do not refrigerate.

Inactive ingredients

citric acid, disodium EDTA, FD&C red #40, glycerin, propyl gallate, propylene glycol, purified water, sodium benzoate, sodium citrate, sorbitol, sucralose, xanthan gum

Questions or comments?

Call 1-877-753-3935 Monday-Friday 9AM-5PM EST

Principal Display Panel

Compare to Delsym® Cough+ ® Chest Congestion DM active ingredients*

MAXIMUM STRENGTH†

Cough & Chest Congestion DM

DEXTROMETHORPHAN HBr

Cough Suppressant

GUAIFENESIN, Expectorant

Controls Cough

Relieves Chest Congestion

Thins & Loosens mucus

Ages 12 & Over

FL OZ (mL)

dosing cup included

†Under OTC monograph.

TAMPER EVIDENT: DO NOT USE IF PRINTED SAFETY SEAL AROUND OR UNDER CAP IS BROKEN OR MISSING.

*This product is not manufactured or distributed by Reckitt Benckiser, distributor of Delsym® Cough+ ® Chest Congestion DM.

Distributed by: CVS Pharmacy, Inc,

One CVS Drive, Woonsocket, RI 02895.

Package Label

CVS Maximum Strength Cough & Chest Congestion DM